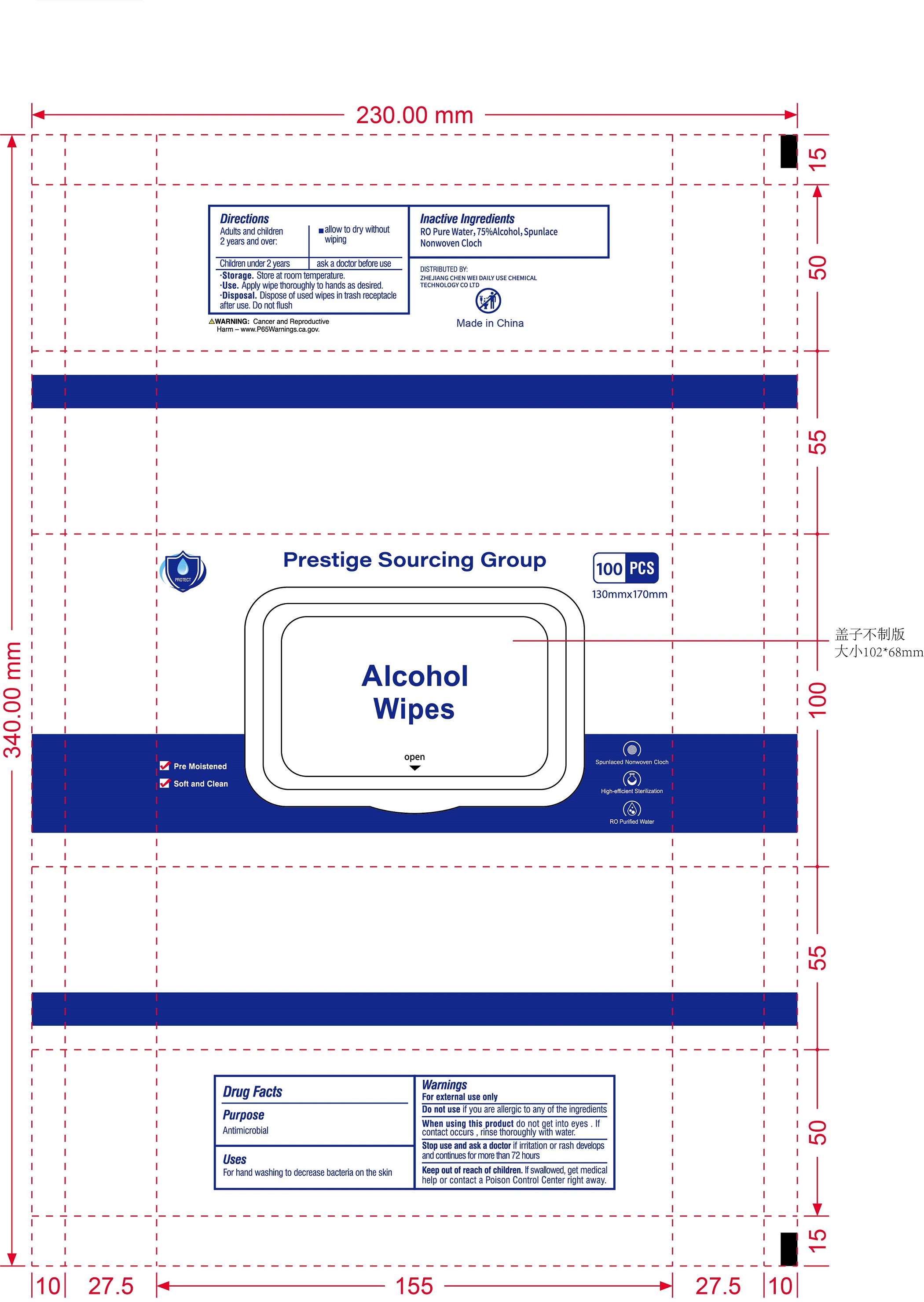 DRUG LABEL: Alcohol  Wipes
NDC: 80213-100 | Form: CLOTH
Manufacturer: Zhejiang Chenwei Daily Chemicals Technology Co.,Ltd.
Category: otc | Type: HUMAN OTC DRUG LABEL
Date: 20200831

ACTIVE INGREDIENTS: ALCOHOL 3 mL/1 1
INACTIVE INGREDIENTS: WATER

80213-100-01 Alcohol Wipes 3ml/1 100抽袋装 Zhejiang Chenwei Daily Chemicals Technology Co.,Ltd.

Active Ingredient(s)

Alcohol 75% v/v. Purpose:Antimicrobial

Purpose

Antimicrobial, Alcohol Wipes

Use

For hand washing to decrease bacteria on the skin.

Warnings

For external use only. F

- Do not use if you are allergic to any of the ingredients.

When using this product do not get into eyes. If contact occurs, rinse thoroughly with water.

Stop use and ask a doctor if irritation or rash develops and continues for more than 72 hours.

Keep out of reach of children. If swallowed, get medical help or contact a Poison Control Center right away.

Directions

- Adults and children 2 years and over.
- allow to dry without wiping.
- Children under 2 years ask a doctor before use.
- Storage. Store at room temperature.
- Use. Apply wipe thoroughly to hands as desired.
- Disposal. Dispose of used wipes in trash receptacle after use. Do not flush.

Other information

- Store at room temperature.

Inactive ingredients

Water

Package Label - Principal Display Panel

100 cloth in 1 BAG NDC: 80213-100-01